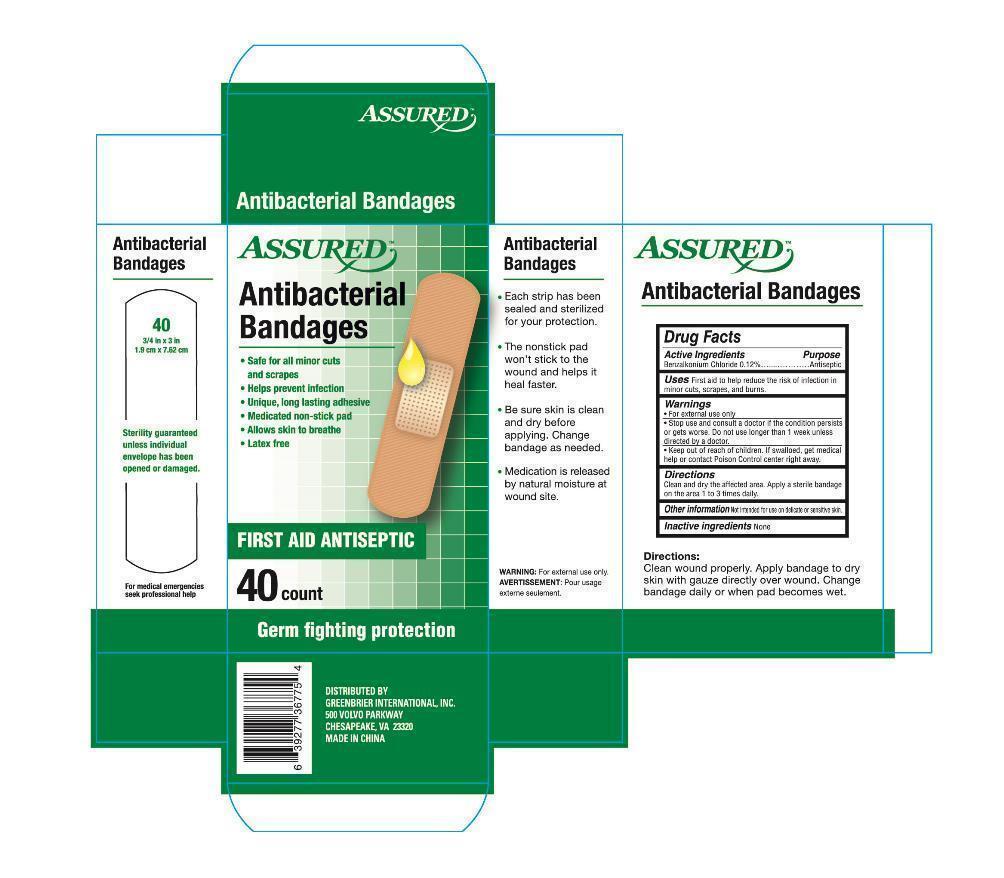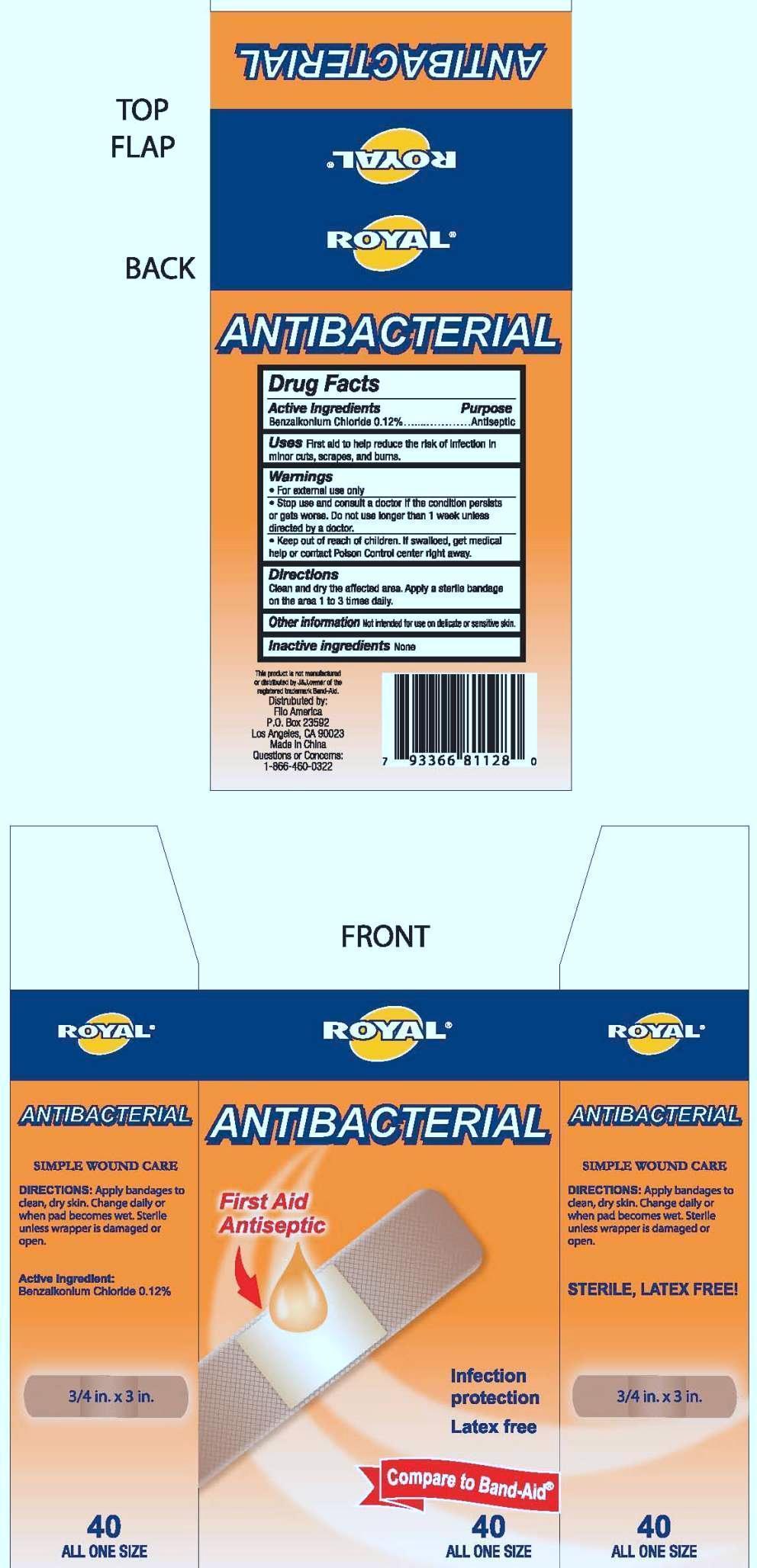 DRUG LABEL: BANDAGE
NDC: 69119-001 | Form: SWAB
Manufacturer: Dongyang Haodi Medical CO.,Ltd 
Category: otc | Type: HUMAN OTC DRUG LABEL
Date: 20140724

ACTIVE INGREDIENTS: BENZALKONIUM CHLORIDE 0.0012 mg/1 mg
INACTIVE INGREDIENTS: COTTON FIBER

Active Ingredients

Benzalkonium Chloride 0.12%

Purpose

Antiseptic

Use

First aid to help reduce the risk of infection in minor cuts ,scrapes,and burns.

Warnings

For external use only.

Stop use and consult a doctor if the dondition persists or gets worse .Do not use longer than 1 week unless directed by a doctor.

Keep out of reach of children.if swallowed get medical help or contact Poison control Center right away.

Directions

Clean and dry the affected area .Apply a sterile bandage on the area 1 to 3 times daily.

Other information :not intended for use on delicate or sensitive skin.

Inactive Ingredient

None